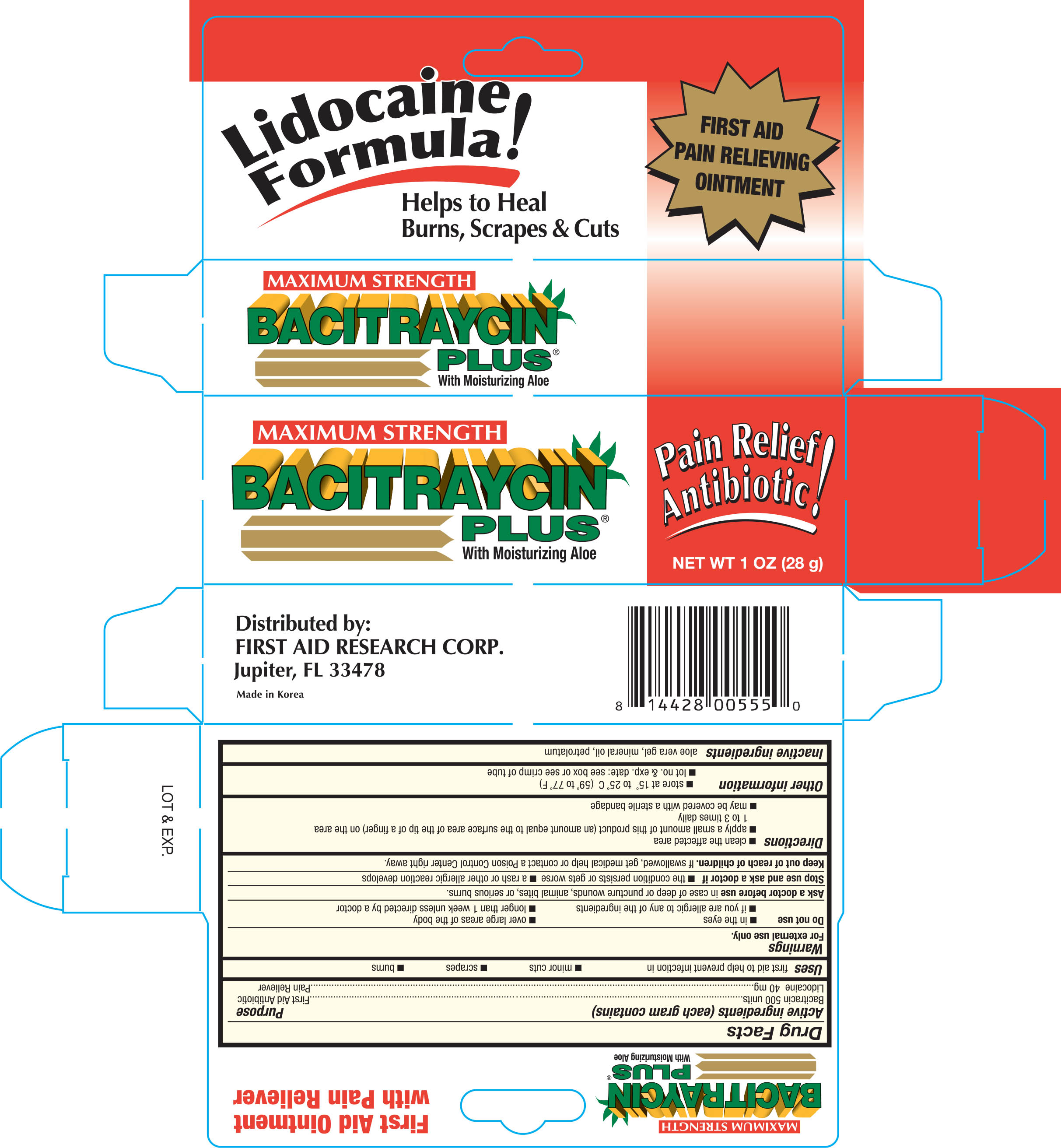 DRUG LABEL: First Aid Macimum Sterngth Bacitraycin Plus
                
NDC: 75983-495 | Form: OINTMENT
Manufacturer: First Aid Research Corp
Category: otc | Type: HUMAN OTC DRUG LABEL
Date: 20170511

ACTIVE INGREDIENTS: BACITRACIN 500 [USP'U]/1 g; LIDOCAINE 40 mg/1 g
INACTIVE INGREDIENTS: ALOE VERA LEAF; MINERAL OIL; PETROLATUM

Active Ingredients (each gram contains) Purpose

Bacitracin 500 units........................................................................First Aid Antibiotic

Lidocaine 40 mg....................................................................................Pain Reliever

Uses

first aid to help prevent infection in

- minor cuts
- scrapes
- burns

Warnings For external use only.

Do not use

- in the eyes
- over large areas of the body
- if you are allergic to any of the ingredients
- longer than 1 week unless directed by a doctor

Ask a doctor before use in case of deep or puncture wounds, animal bites, or serious burns.

Stop use and ask a doctor if

- the condition persists or gets worse
- a rash or other allergic reaction develops

Keep out of reach of children

If swallowed, get medical help or contact a Poison Control Center right away.

Directions

- clean the affected area
- apply a small amount of this product (an amount equal to the surface area of the tip of a finger) on the area 1 to 3 times daily
- may be covered with a sterile bandage

Other information

- store at 15° to 25° C (59° to 77°F)
- Lot No. and Exp. Date: see box or see crimp of tube

Inactive ingredients

aloe vera gel, mineral oil and petrolatum

DOSAGE AND ADMINISTRATION

Distributed By:

First Aid Research Corp.

3375 Park Ave. Suite 2003

Wantagh, NY 11793 U.S.A.

Made in Korea